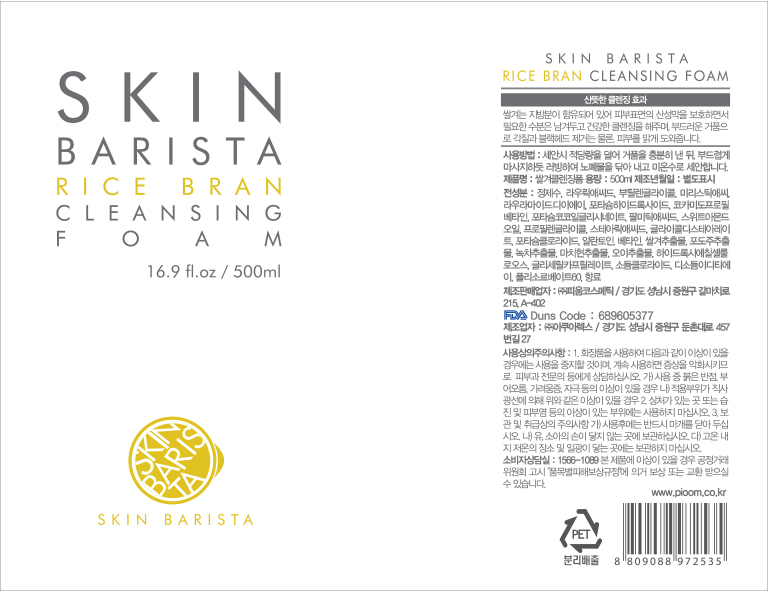 DRUG LABEL: Skin Barista Rice Bran Cleansing Foam
NDC: 70441-0002 | Form: LIQUID
Manufacturer: Pioom Cosmetic Co.,ltd
Category: otc | Type: HUMAN OTC DRUG LABEL
Date: 20250115

ACTIVE INGREDIENTS: ALLANTOIN 0.3 g/100 mL
INACTIVE INGREDIENTS: BUTYLENE GLYCOL; WATER

Drug Facts

ACTIVE INGREDIENT

allantoin

INACTIVE INGREDIENT

water, butylene glycol, etc.

PURPOSE

skin protectant

keep out of reach of the children

INDICATIONS AND USAGE

apply proper amount to the skin

WARNINGS

1. Do not use in the following cases(Eczema and scalp wounds)
2.Side Effects
1)Due to the use of this druf if rash, irritation, itching and symptopms of hypersnesitivity occur dicontinue use and consult your phamacisr or doctor
3.General Precautions
1)If in contact with the eyes, wash out thoroughty with water If the symptoms are servere, seek medical advice immediately
2)This product is for exeternal use only. Do not use for internal use
4.Storage and handling precautions
1)If possible, avoid direct sunlight and store in cool and area of low humidity
2)In order to maintain the quality of the product and avoid misuse
3)Avoid placing the product near fire and store out in reach of children

DOSAGE AND ADMINISTRATION

for external use only